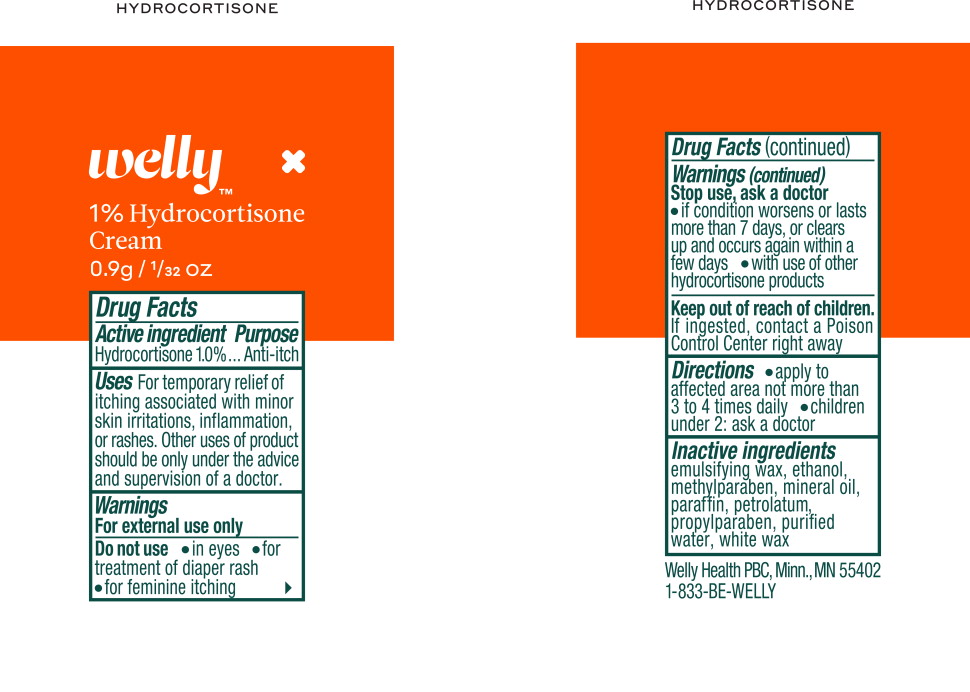 DRUG LABEL: Anti-itch
NDC: 72663-580 | Form: CREAM
Manufacturer: Welly Health PCB
Category: otc | Type: HUMAN OTC DRUG LABEL
Date: 20190225

ACTIVE INGREDIENTS: hydrocortisone 1 g/1 mL
INACTIVE INGREDIENTS: alcohol; methylparaben; mineral oil; paraffin; petrolatum; propylparaben; water; white wax

Drug Facts

Active ingredient

Hydrocortisone 1.0%

Purpose

Anti-itch

Uses

For temporary relief of itching associated with minor skin irritations, inflammation, or rashes. Other uses of product should be only under the advice and supervision of a doctor.

Warnings

External use only

Do not use

- in eyes
- for treatment of diaper rash
- for feminine itching

Stop use, ask a doctor

- if conditions worsen or lasts more than 7 days, or clears up and occurs again within a few days
- with use of other hydrocortisone products

Keep out of reach of children.

If ingested, contact a Poison Control Center right away

Directions

- apply to affected area not more than 3 to 4 times daily
- children under 2: ask a doctor

Inactive ingredients

emulsifying wax, ethanol, methylparaben, mineral oil, paraffin, petrolatum, propylparaben, purified water, white wax

Welly Health PBC, Minn., MN 55402

1-833-BE-WELLY

Principal Display Panel - Welly Health Hydrocortisone Cream Pouch Label

Welly™

1% Hydrocortisone
Cream

0.9g/ 1/32 OZ